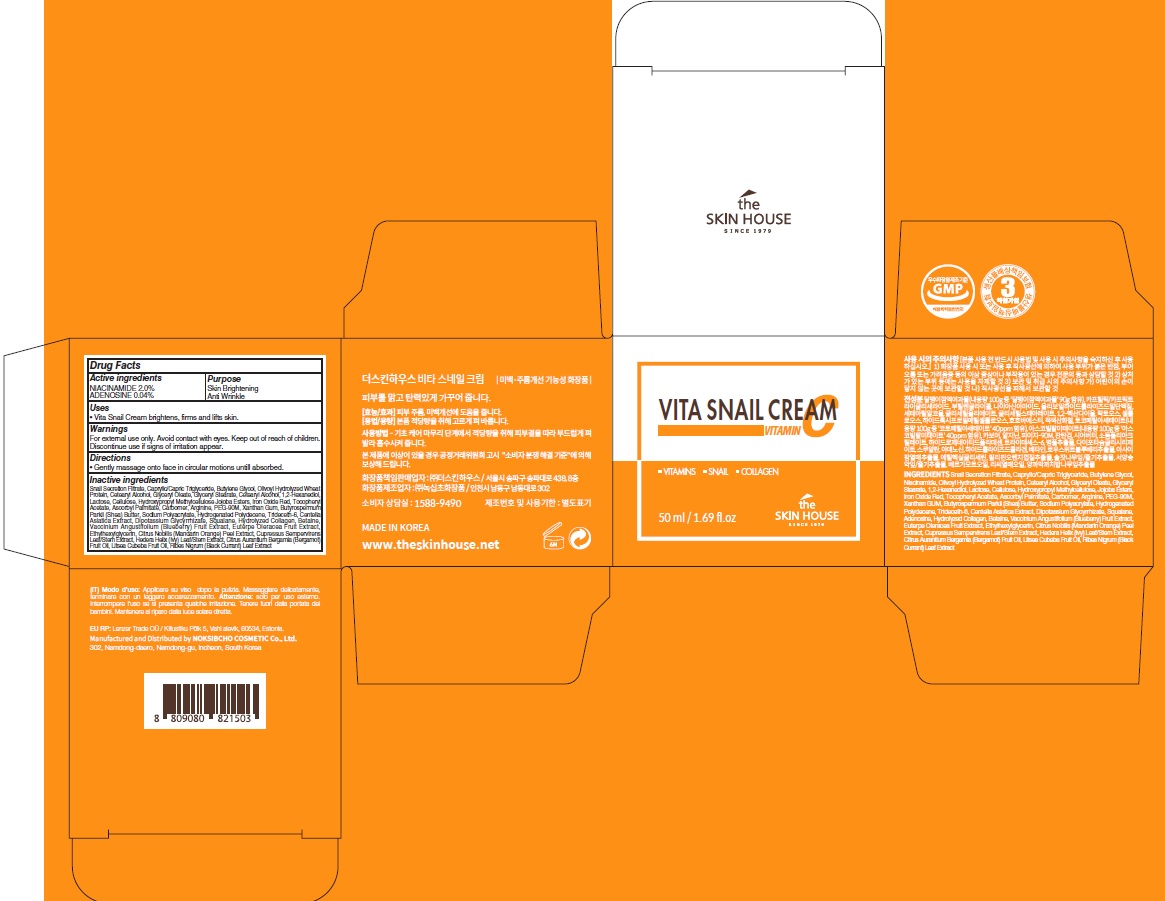 DRUG LABEL: VITA SNAIL
NDC: 73590-0061 | Form: CREAM
Manufacturer: NOKSIBCHO cosmetic Co., Ltd.
Category: otc | Type: HUMAN OTC DRUG LABEL
Date: 20210303

ACTIVE INGREDIENTS: NIACINAMIDE 1.0 g/50 mL; ADENOSINE 0.02 g/50 mL
INACTIVE INGREDIENTS: MEDIUM-CHAIN TRIGLYCERIDES; Butylene glycol; CETOSTEARYL ALCOHOL; Glyceryl Oleate

Drug Facts

ACTIVE INGREDIENTS

NIACINAMIDE 2.0%
ADENOSINE 0.04%

INACTIVE INGREDIENTS

Snail Secretion Filtrate, Caprylic/Capric Triglyceride, Butylene glycol, Olivoyl Hydrolyzed Wheat Protein, Cetearyl Alcohol, Glyceryl Oleate, Glyceryl Stearate, Cetearyl Alcohol, 1,2-Hexanediol, Lactose, Cellulose, Hydroxypropyl Methylcellulose Jojoba Esters, Iron Oxide Red, Tocopheryl Acetate, Ascorbyl Palmitate, Carbomer, Arginine, PEG-90M, Xanthan GUM, Butyrospermum Parkii (Shea) Butter, Sodium Polyacrylate, Hydrogenated polydecene, Trideceth-6, Centella Asiatica Extract, Dipotassium Glycyrrhizate, Squalane, Hydrolyzed Collagen, Betaine, Vaccinium Angustifolium (Blueberry) Fruit Extract, Euterpe Oleracea Fruit Extract, Ethylhexylglycerin, Citrus Nobilis (Mandarin Orange) Peel Extract, Cupressus Sempervirens Leaf/Stem Extract, Hedera Helix (Ivy) Leaf/Stem Extract, Citrus Aurantium Bergamia (Bergamot) Fruit Oil, Litsea Cubeba Fruit Oil, Ribes Nigrum (Black Currant) Leaf Extract

PURPOSE

Skin Brightening
Anti wrinkle

WARNINGS

For external use only. Avoid contact with eyes. Keep out of reach of children. Discontinue use if signs of irritation appear.

KEEP OUT OF REACH OF CHILDREN

keep out of reach of the children

Uses

■ Vita Snail Cream brightens, fi¬rms and lifts skin.

Directions

■ Gently massage onto face in circular motions untill absorbed.